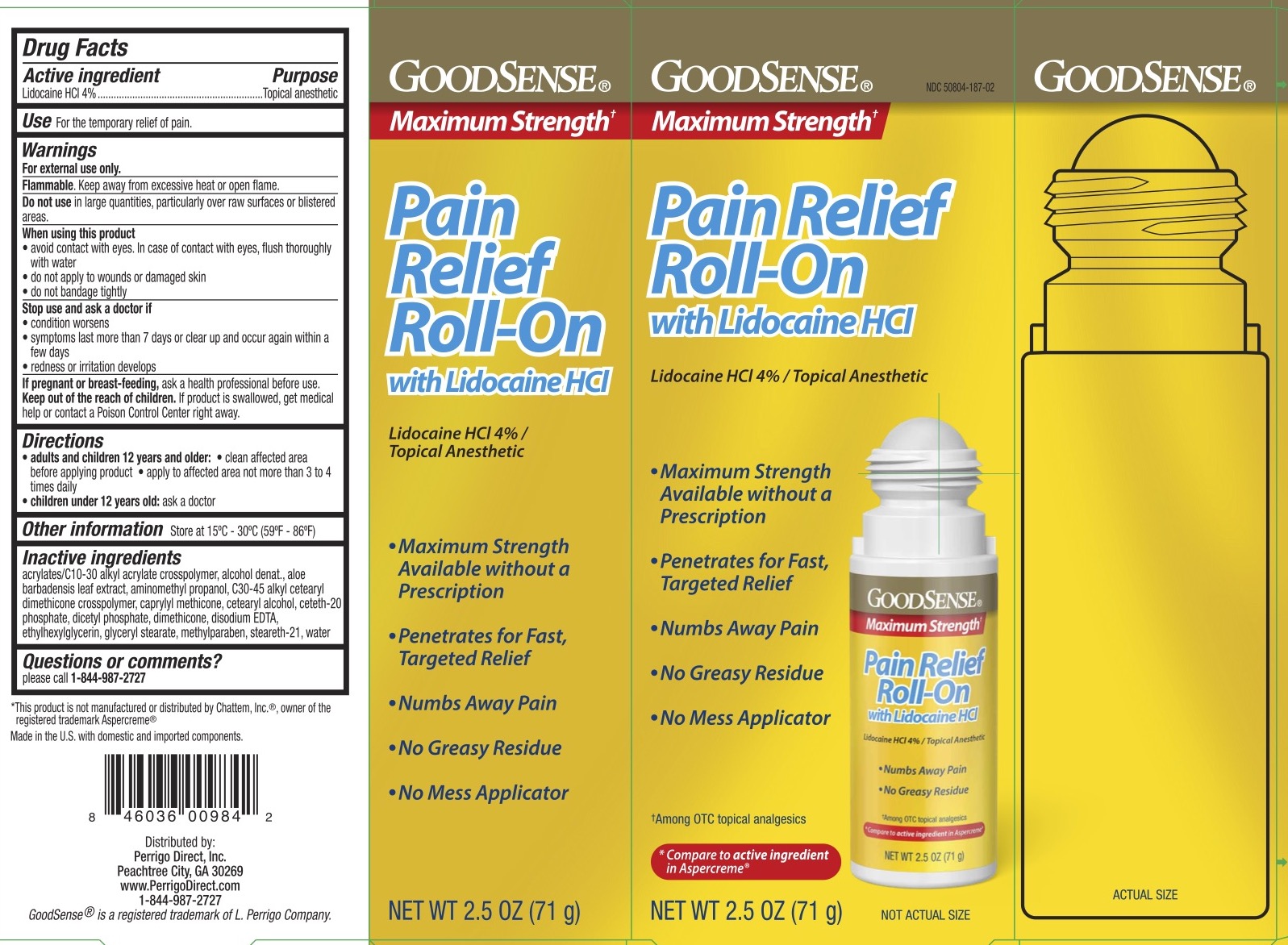 DRUG LABEL: Good Sense Pain Relief Roll On
NDC: 50804-187 | Form: LIQUID
Manufacturer: Geiss, Destin & Dunn, Inc
Category: otc | Type: HUMAN OTC DRUG LABEL
Date: 20250808

ACTIVE INGREDIENTS: LIDOCAINE HYDROCHLORIDE 4 g/100 g
INACTIVE INGREDIENTS: WATER; GLYCERIN; ACRYLATES/C10-30 ALKYL ACRYLATE CROSSPOLYMER (60000 MPA.S); ALCOHOL; AMINOMETHYL PROPANOL; C30-45 ALKYL CETEARYL DIMETHICONE CROSSPOLYMER; ALOE VERA LEAF; CETEARYL ALCOHOL; CETETH-20 PHOSPHATE; DICETYL PHOSPHATE; DIMETHICONE 200; EDETATE DISODIUM; STEARETH-21; GLYCERYL STEARATE; METHYLPARABEN; ETHYLHEXYLGLYCERIN

GoodSense Pain Relief Roll-on

ACTIVE INGREDIENT

Lidocaine HCl 4%

PURPOSE

Topical anesthetic

INDICATIONS AND USAGE

For the temporary relief of pain

WARNINGS

For external use only.

Flammable. Keep away from excessive heat or open flame.

Do not use in large quantities, particularly over raw surfaces or blistered areas.

When using this product avoid contact with eyes. Rinse with water if contact occurs. Do not apply to wounds or damaged skin. Do not bandage tightly.

Stop use and ask a doctor if the condition worsens or symptoms persist for more than 7 days or clear up and occur again within a few days, and redness or irritation develops.

DOSAGE AND ADMINISTRATION

Adults and children 12 years and older: clean affected area before applying products, apply to affected area not more than 3 to 4 times daily.

Children under 12 years old: ask a doctor.

Keep out of reach of children. If the product is swallowed, get medical help or contact a Poison Control Center right away.

PREGNANCY OR BREAST FEEDING

Ask a health professional before use.

INACTIVE INGREDIENT

Acrylates/C10-30 alkyl acrylate crosspolymer, alcohol denat., aloe barbadensis leaf extract, aminomethyl propanol, C30-45 alkyl cetearyl dimethicone crosspolymer, caprylyl methicone, cetearyl alcohol, ceteth-20 phosphate, dicetyl phosphate, dimethicone, disodium EDTA, ethylhexylglycerin, glycerin stearate, methylparaben, steareth-21, water.